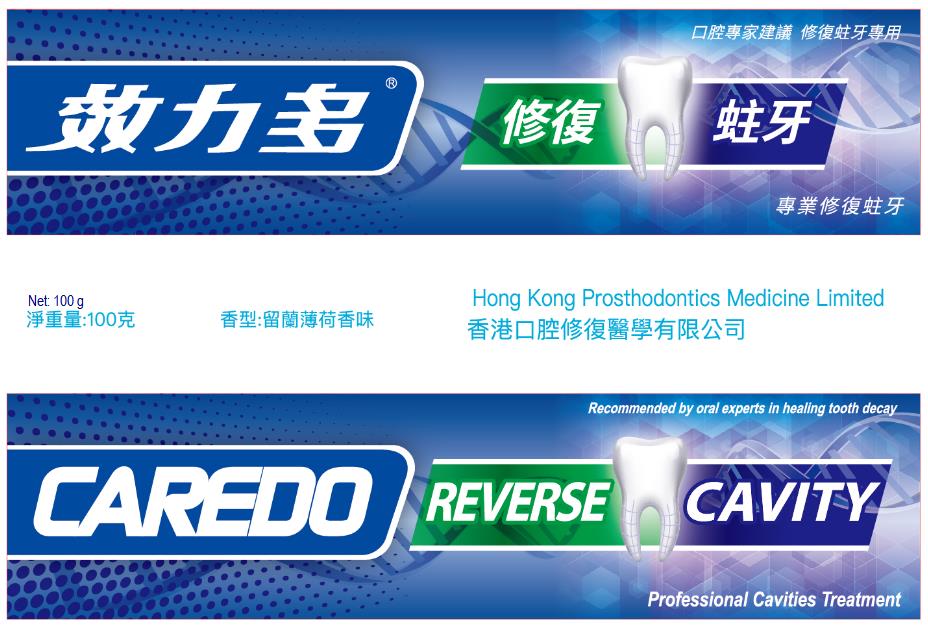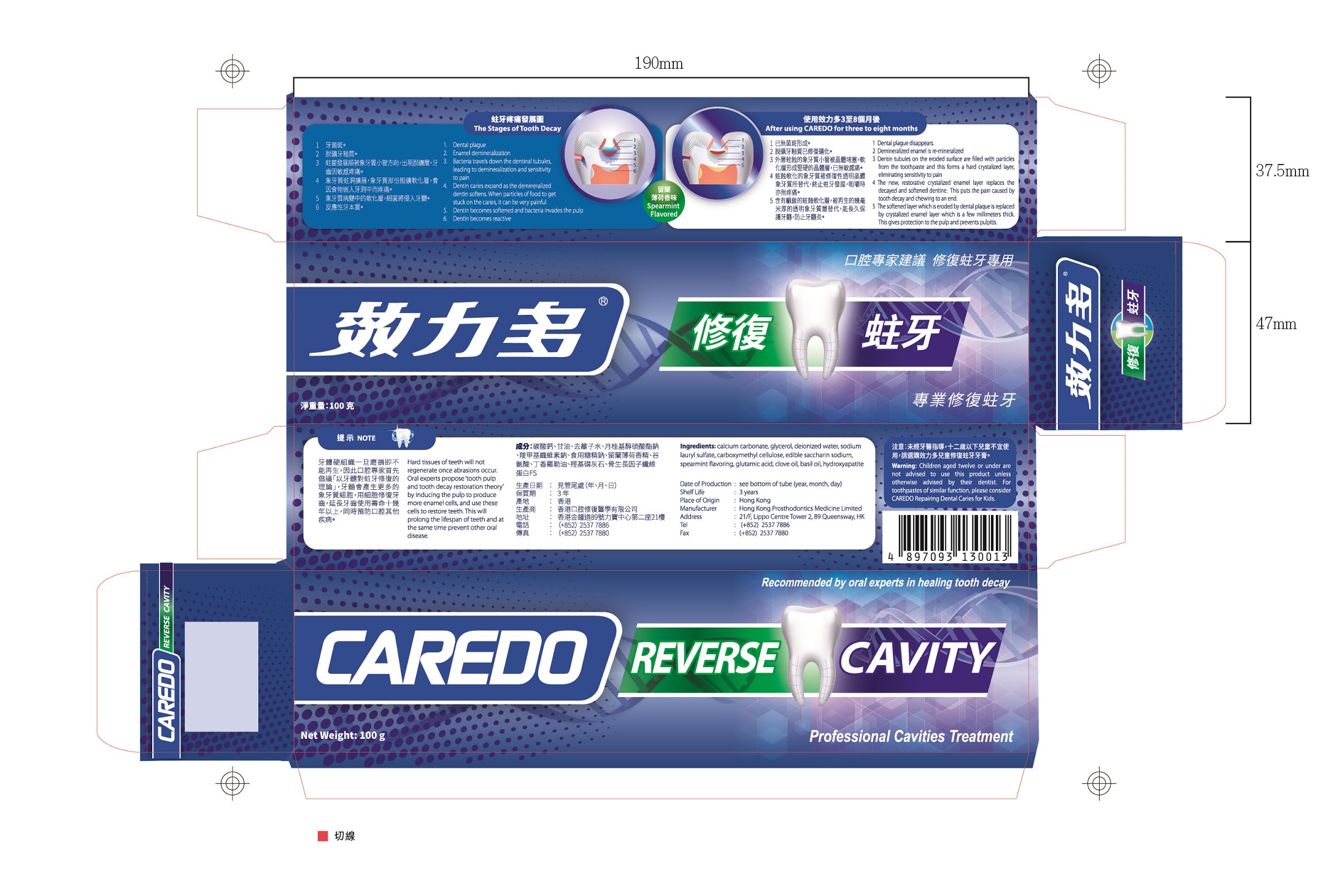 DRUG LABEL: CAREDO Professional Cavities Treatment Toothpastes
NDC: 72415-231 | Form: PASTE, DENTIFRICE
Manufacturer: Hong Kong Prosthodontics Medicine Limited
Category: otc | Type: HUMAN OTC DRUG LABEL
Date: 20180815

ACTIVE INGREDIENTS: CALCIUM PHOSPHATE, UNSPECIFIED FORM 0.5 g/100 g
INACTIVE INGREDIENTS: CARBOXYMETHYLCELLULOSE 1 g/100 g; WATER 14.3 g/100 g; CALCIUM CARBONATE 50 g/100 g; SACCHARIN SODIUM 0.1 g/100 g; SODIUM LAURYL SULFATE 2 g/100 g; GLYCERIN 30 g/100 g; BASIL OIL 0.1 g/100 g; SPEARMINT OIL 1.5 g/100 g; GLUTAMIC ACID 0.5 g/100 g

CAREDO Professional Cavities Treatment Toothpaste, 100g

Active ingredient

hydroxyapatite (0.5%): 0.5g/package.

Inactive ingredient

calcium carbonate (50%): 50g/package;

glycerol (30%): 30g/package;
deionized water (14.3%): 14.3g/package;
sodium lauryl sulfate (2%): 2g/package;
carboxymethyl cellulose (1%): 1g/package;
edible saccharin sodium (0.1%): 0.1g/package;
spearmint flavoring (1.5%): 1.5g/package;

glutamic acid (0.5%): 0.5g/package;

clove oil basil oil (0.1%): 0.1g/package.

Purpose

Treatment of dental plague, enamel dernineralization, bacteria, etc.

When using

When tooth occur dental plague, enamel dernineralization, bacteria, etc..

Do not use when oral infection.
It should be cautiously used if you are kind of allergic constitution or you have inflammation.

Stop use

If irritation or discomfort occurs, discontinue the use and consult a physician.

Ask doctor

If irritation or discomfort occurs, discontinue the use and consult a physician.

Ask doctor/pharmacist when you current use other drugs.

Keep out of reach of children

Questions

Please contact us when you have any questions.

Pregnancy or breast feeding

Pregnant or breast feeding women shall follow doctor advice.

Indications & usage

Apply properly this product on the toothbrush, and brush tooth as like common do.

Dosage & administration

One tube of 100g in one package.

Dosage forms & strengths

It is paste form.
Apply proper as you need.

Warnings

Children aged twelve or under are not advised to use this product unless otherwise advised by their dentist.

Package label. Principal display panel

---

Container Label

---

---

Package Label

---